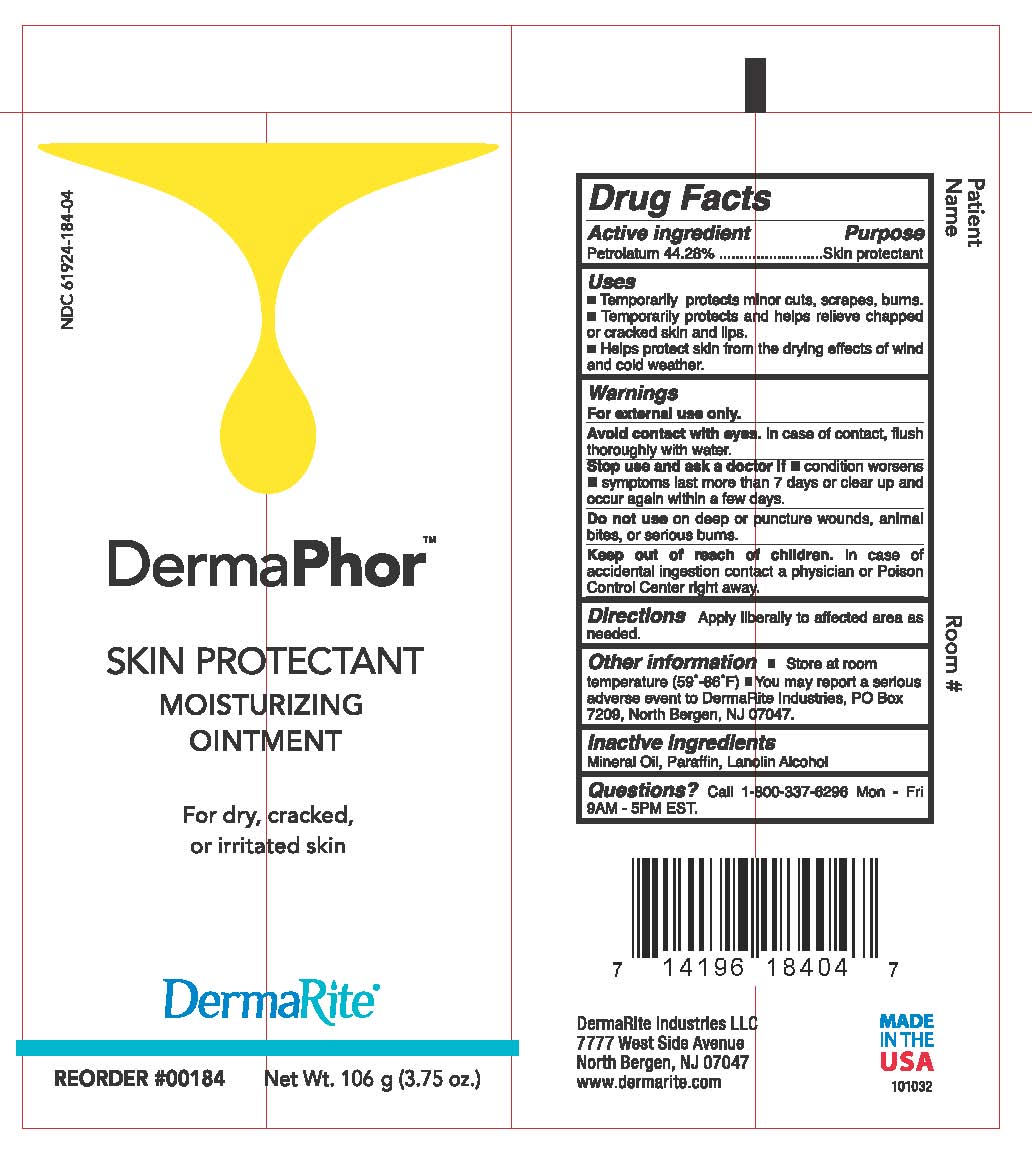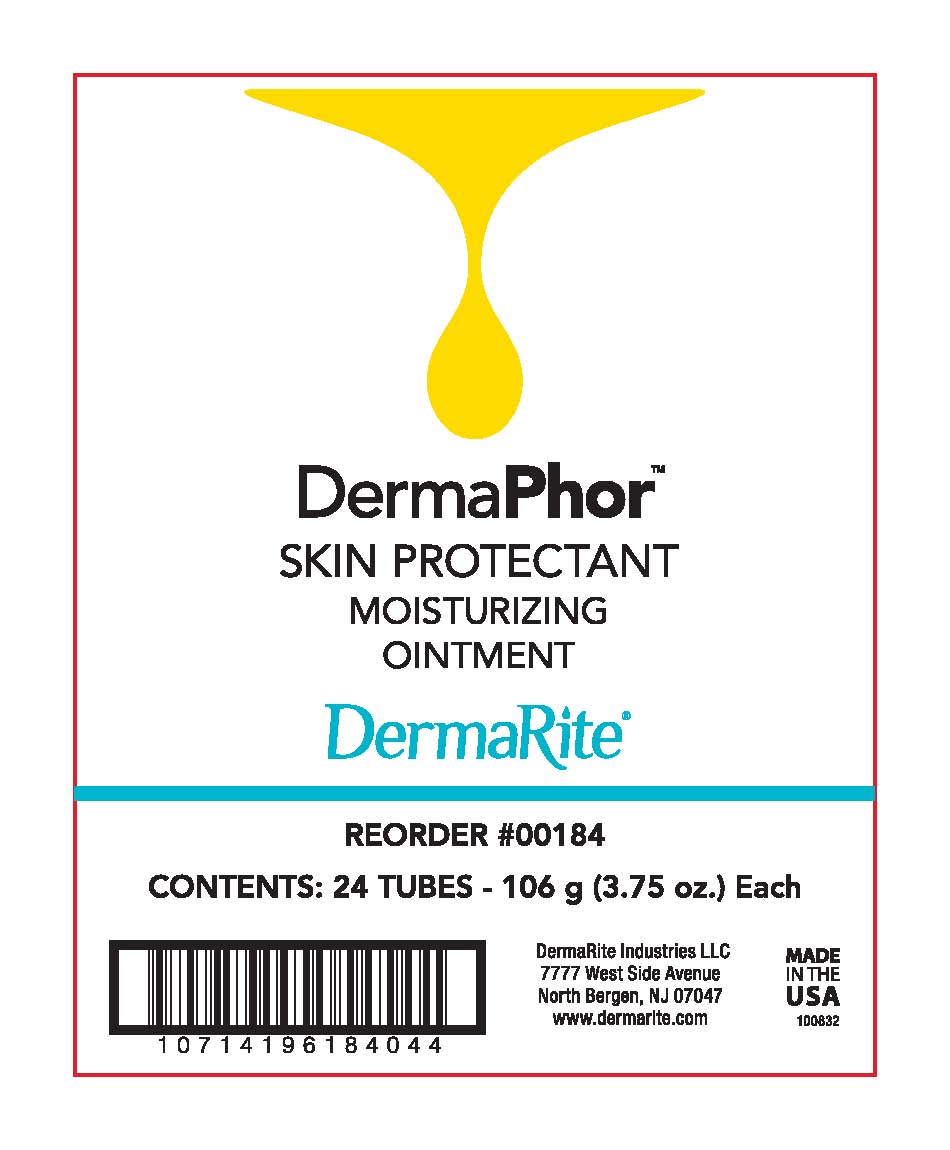 DRUG LABEL: Dermaphor
NDC: 61924-184 | Form: OINTMENT
Manufacturer: DermaRite Industries, LLC
Category: otc | Type: HUMAN OTC DRUG LABEL
Date: 20241205

ACTIVE INGREDIENTS: PETROLATUM 44 g/100 g
INACTIVE INGREDIENTS: MINERAL OIL; LANOLIN ALCOHOLS; PARAFFIN

DERMAPHOR

Active Ingredient:

Petrolatum 44.28%

Purpose:

Skin Protectant

Uses:

- Temporarily protects minor cuts, scrapes, burns.
- Temporarily protects and helps relieve chapped or cracked skin and lips.
- Helps protect skin from the drying effects of wind and cold weather.

Warnings:

For external use only.

Warnings:

Avoid contact with eyes. In case of contact, flush thoroughly with water.

Warnings:

Stop and ask a doctor if

- condition worsens
- symptoms last more than 7 days or clear up and occur again within a few days

Warnings:

Do not use on deep or puncture wounds, animal bites, or serious wounds.

Warnings:

Keep out of reach of children.

Incase of accidental ingestion contact a Physician or Poison Control Center right away.

Directions:

Apply liberally to affected area as needed.

Other Information:

- Store at room temperature (59º- 86ºF)
- You may report a serious adverse event to DermaRite Industries, PO Box 7209, North Bergen, NJ 07047.

Inactive Ingredients:

Mineral Oil, Paraffin, Lanolin Alcohol

Questions?:

Call 800-337-6296 Mon - Fri 9AM - 5PM EST.